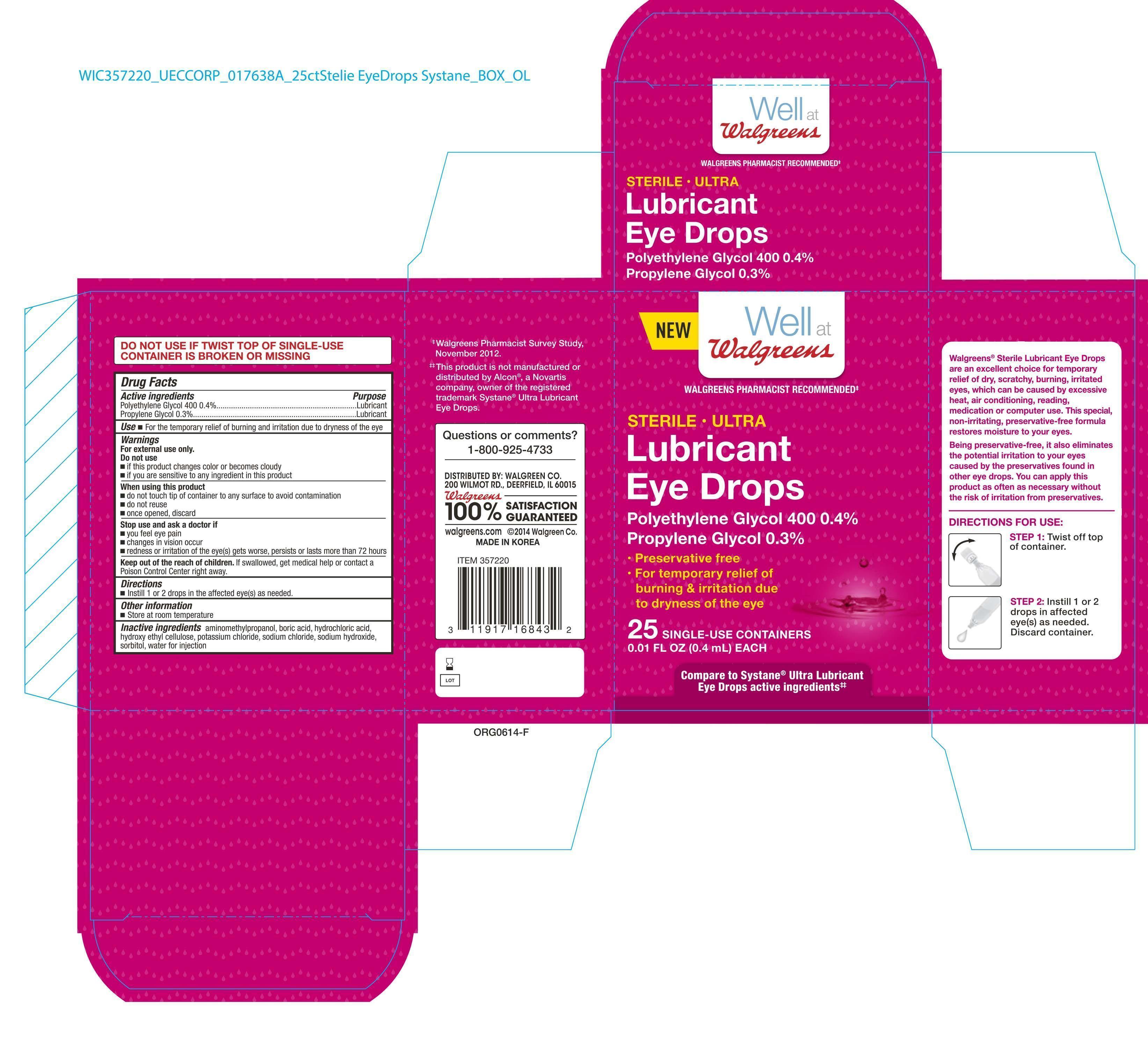 DRUG LABEL: Walgreens Lubricant Eye Drops
NDC: 0363-7220 | Form: SOLUTION/ DROPS
Manufacturer: Walgreen Company
Category: otc | Type: HUMAN OTC DRUG LABEL
Date: 20140806

ACTIVE INGREDIENTS: POLYETHYLENE GLYCOL 400 0.4 mg/100 mg; PROPYLENE GLYCOL 0.3 mg/100 mg
INACTIVE INGREDIENTS: AMINOMETHYLPROPANOL; BORIC ACID; HYDROCHLORIC ACID; HYDROXYETHYL CELLULOSE (100 MPA.S AT 2%); POTASSIUM CHLORIDE; SODIUM CHLORIDE; SODIUM HYDROXIDE; SORBITOL; WATER

Active Ingredient Purpose

Polyethylene Glycol 400 0.4%----------------------------------------------- Lubricant

Propylene Glycol 0.3%------------------------------------------------------- Lubricant

Use

- For the temporary relief of burning and irritation due to dryness of the eye

Warnings:

For external use only.

Do not use

- if this product changes color or becomes cloudy
- if you are sensitive to any ingredient in this product

When using this product

- do not touch tip of container to any surface to avoid contamination
- do not reuse
- once opended, discard

Stop use and ask a doctor if

- you feel eye pain
- changes in vision occur
- redness or irritation of the eye(s) gets worse, persists or lasts more than 72 hours

KEEP OUT OF REACH OF CHILDREN

Keep out of the reach of chilren. If swallowed, get medical help or contact a Poison Control Center right away.

Directions

- Instill 1 or 2 drops in the affected eye(s) as needed.

Other information

- Store at room temperature

Inactive Ingredients

aminomethylpropanol, boric acid, hydrochloric acid, hydroxy ethyl cellulose, potassium chloride, sodium chloride, sodium hydroxide, sorbitol, water for injection

DOSAGE AND ADMINISTRATION

DISTRIBUTED BY:

WALGREEN CO.

200 WILMOT RD.,

DEERFIELD, IL 60015